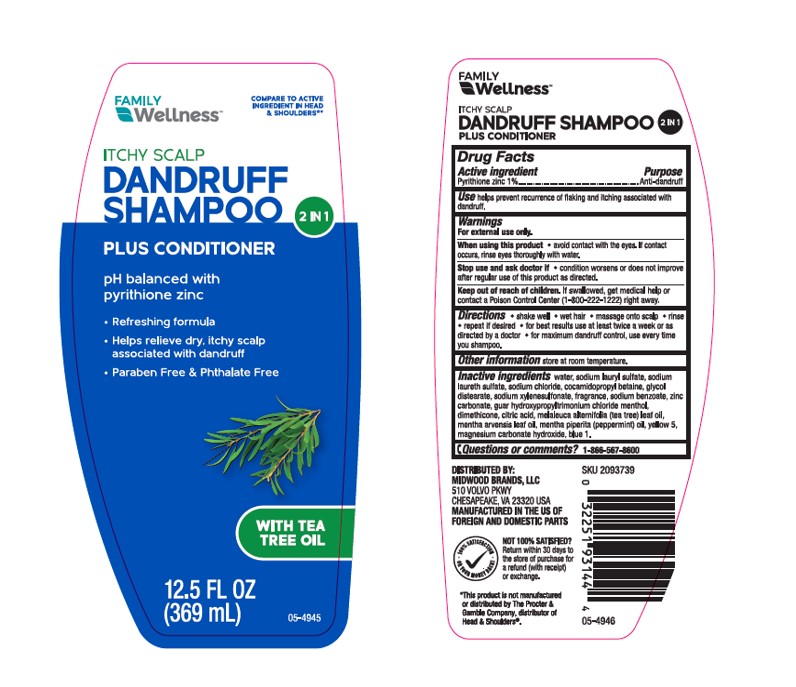 DRUG LABEL: Walgreens Dandruff Conditioner 2 in 1 Itchy Scalp
NDC: 55319-444 | Form: SHAMPOO
Manufacturer: FAMILY DOLLAR SERVICES INC
Category: otc | Type: HUMAN OTC DRUG LABEL
Date: 20251208

ACTIVE INGREDIENTS: Pyrithione Zinc 10 mg/1 mL
INACTIVE INGREDIENTS: Water; SODIUM LAURETH-3 SULFATE; Sodium Lauryl Sulfate; Glycol Distearate; Sodium Chloride; Sodium Xylenesulfonate; Cocamidopropyl Betaine; Dimethicone; Sodium Benzoate; GUAR HYDROXYPROPYLTRIMONIUM CHLORIDE; Magnesium Carbonate Hydroxide; APPLE JUICE; Glycerin; SODIUM METABISULFITE; CITRIC ACID MONOHYDRATE; Methylchloroisothiazolinone; Methylisothiazolinone; FD&C YELLOW NO. 5; FD&C BLUE NO. 1

Walgreens Dandruff Shampoo & Conditioner 2 in 1 Itchy Scalp
Anti-dandruff

Drug Facts

Active ingredient

Pyrithione Zinc 1%

Purpose

Anti-dandruff

Use

helps prevent recurrence of flaking and itching associated with dandruff.

Warnings

For external use only

When using this product

- avoid contact with the eyes. If contact occurs, rinse eyes thoroughly with water.

Stop use and ask a doctor if

- condition worsens or does not improve after regular use as directed.

Keep out of reach of children. If swallowed, get medical help or contact a Poison Control Center (1-800-222-1222) right away.

Directions

- shake well
- wet hair
- massage onto scalp
- rinse
- repeat if desired
- for best results use at least twice a week or as directed by a doctor
- for maximum dandruff control, use every time you shampoo.

Other information

store at room temperature

Inactive ingredients

water, sodium laureth sulfate, sodium lauryl sulfate, glycol distearate, sodium chloride, sodium xylenesulfonate, cocamidopropyl betaine, dimethicone, fragrance, sodium benzoate, guar hydroxypropyltrimonium chloride, magnesium carbonate hydroxide, pyrus malus (apple) juice, glycerin, sodium metabisulfite, citric acid, methylchloroisothiazolinone, methylisothiazolinone, yellow 5, blue 1.

Questions or Comments?

1-866-567-8600

DISTRIBUTED BY:

MIDWOOD BRANDS, LLC

510 VOLVO PKWY

CHESAPEAKE, VA 23320 USA

PRINCIPAL DISPLAY PANEL - 369 mL Bottle Label

FAMILY WELLNESS

Compare to the active ingredient
in Head & Shoulders®*

ITCHY SCALP

DANDRUFF

SHAMPOO

2 IN 1

PLUS CONDITIONER

pH balanced

pyrithione zinc

- Refreshing formula
- Helps relieve dry, itchy scalp
  associated with dandruff
- Paraben Free & Phthalate Free

WITH TEA TREE OIL

05-4945

12.5 FL OZ (369 mL)

FAMILY WELLNESS TEA TREE